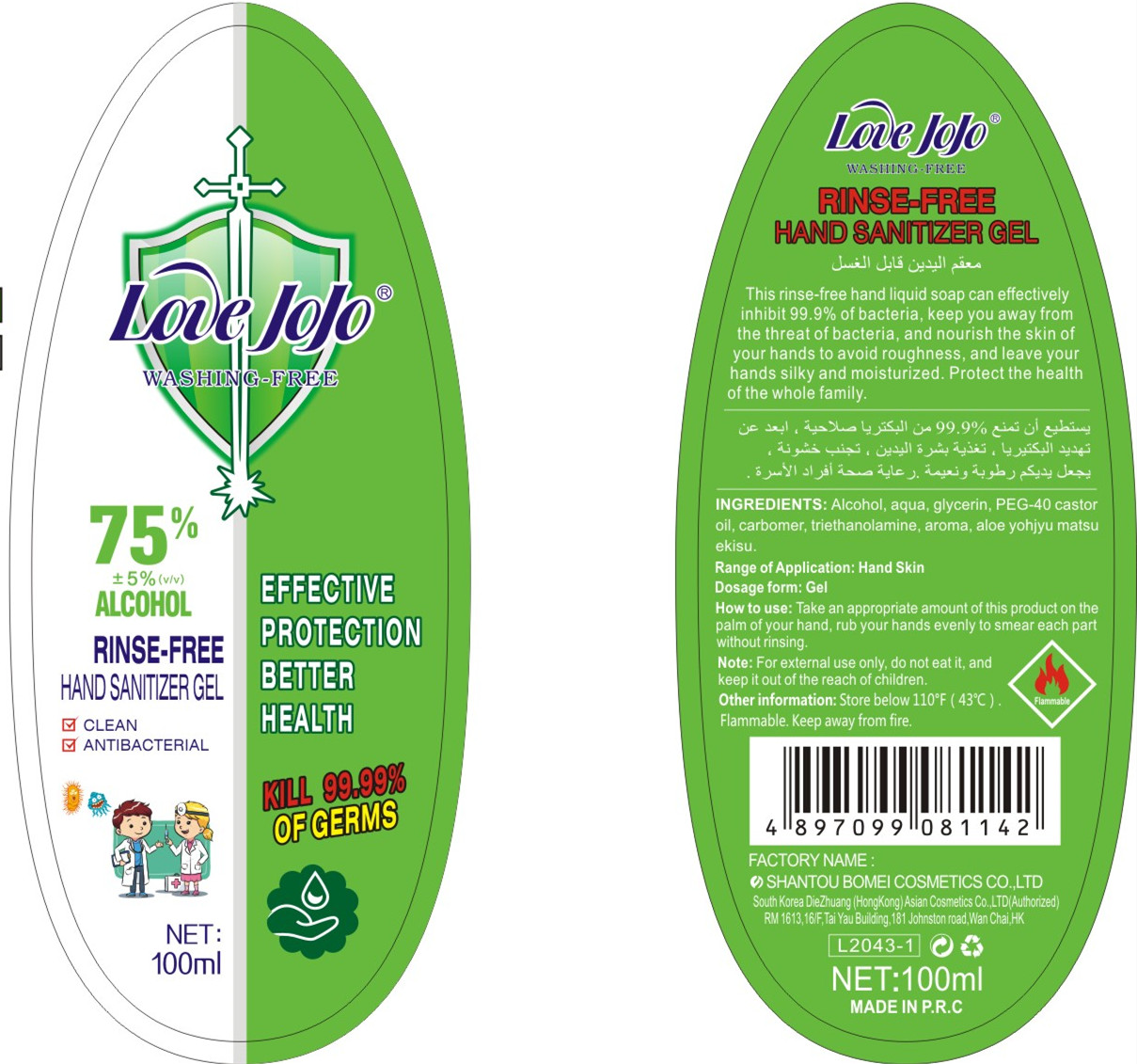 DRUG LABEL: Hand sanitizer gel
NDC: 42085-002 | Form: GEL
Manufacturer: SHANTOU BOMEI COSMETICS CO., LTD.
Category: otc | Type: HUMAN OTC DRUG LABEL
Date: 20200424

ACTIVE INGREDIENTS: ALCOHOL 75 mL/100 mL
INACTIVE INGREDIENTS: PEG-40 CASTOR OIL; TROLAMINE; AROMADENDRIN; ALOE; WATER; GLYCERIN; CARBOMER HOMOPOLYMER, UNSPECIFIED TYPE

DOSAGE AND ADMINISTRATION

Store below 110°F (43°C).Flammable. Keep away from fire.

INACTIVE INGREDIENT

AQUA、GLYCERIN、PEG-40 CASTOR OIL、CARBOMER、TRIETHANOLAMINE、AROMA、ALOE YOHJYU MATSU EKISU

INDICATIONS AND USAGE

Take an appropriate amount of this product on the palm of your hand, rub your hands evenly to smear each part without rinsing.

ACTIVE INGREDIENT

ALCOHOL

keep out of children

PURPOSE

Disinfection
Sterilization
No Rinseing

WARNINGS

For external use only, do not eat it,and keep it out of the reach of children.